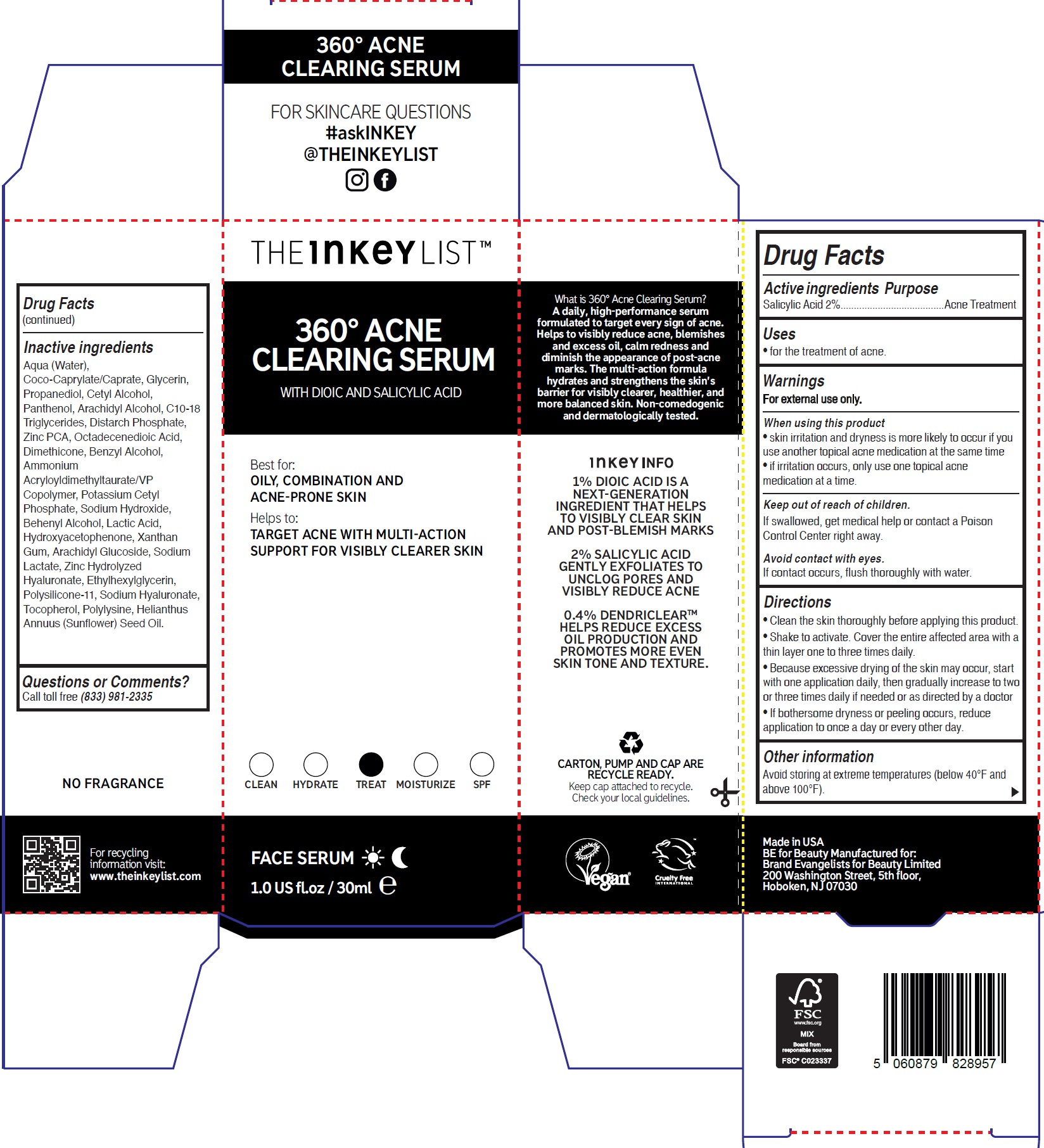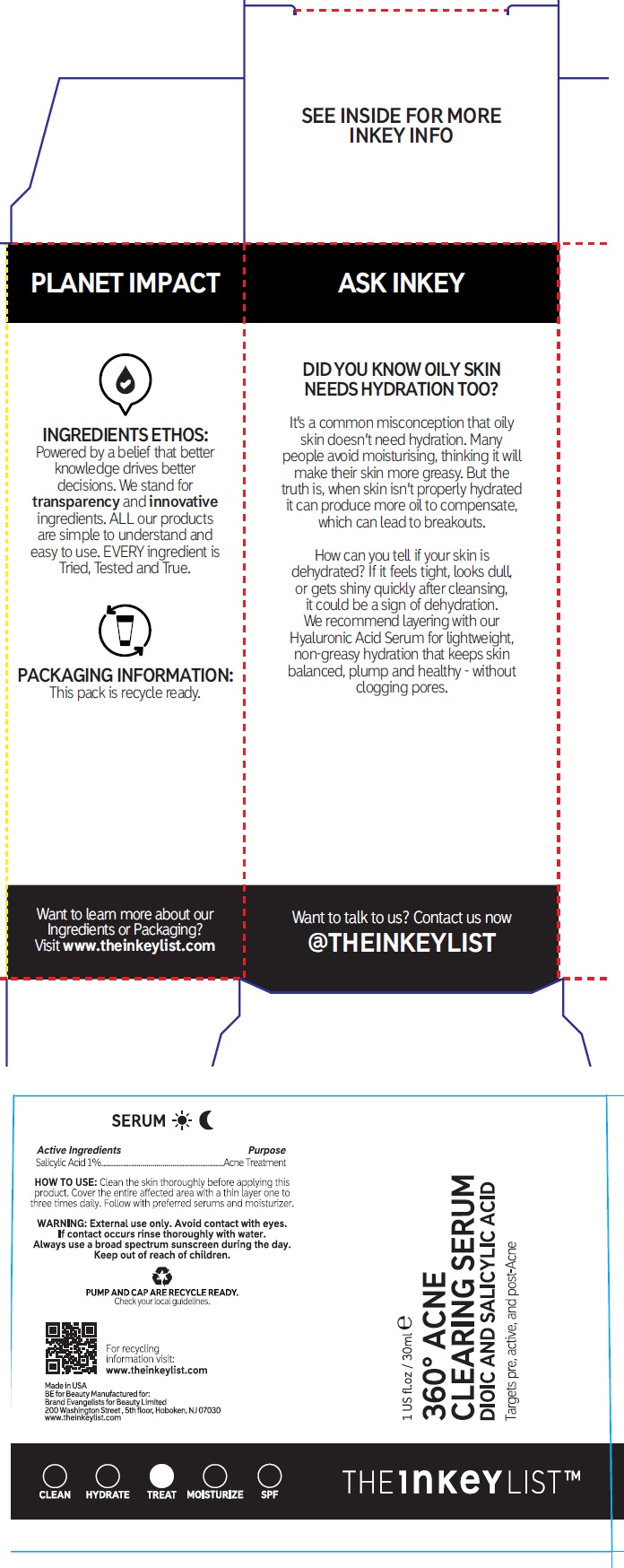 DRUG LABEL: The Inkey List 360 Acne Clearing Serum
NDC: 81136-028 | Form: EMULSION
Manufacturer: Brand Evangelists for Beauty Limited
Category: otc | Type: HUMAN OTC DRUG LABEL
Date: 20250725

ACTIVE INGREDIENTS: SALICYLIC ACID 20 mg/1 mL
INACTIVE INGREDIENTS: WATER; COCOYL CAPRYLOCAPRATE; GLYCERIN; PROPANEDIOL; CETYL ALCOHOL; PANTHENOL; ARACHIDYL ALCOHOL; C10-18 TRIGLYCERIDES; ZINC PIDOLATE; OCTADECENEDIOIC ACID; DIMETHICONE; BENZYL ALCOHOL; AMMONIUM ACRYLOYLDIMETHYLTAURATE/VP COPOLYMER; POTASSIUM CETYL PHOSPHATE; SODIUM HYDROXIDE; BEHENYL ALCOHOL; LACTIC ACID; HYDROXYACETOPHENONE; XANTHAN GUM; ARACHIDYL GLUCOSIDE; SODIUM LACTATE; ETHYLHEXYLGLYCERIN; DIMETHICONE/VINYL DIMETHICONE CROSSPOLYMER (SOFT PARTICLE); SODIUM HYALURONATE; TOCOPHEROL; SUNFLOWER OIL

The Inkey List 360 Acne Clearing Serum

Active ingredients

Salicylic Acid 2%

Purpose

Acne Treatment

Uses

- for the treatment of acne.

Warnings

For external use only.

When using this product

• skin irritation and dryness is more likely to occur if you use another topical acne medication at the same time
• if irritation occurs, only use one topical acne medication at a time.

Keep out of reach of children.

If swallowed, get medical help or contact a Poison Control Center right away.

Avoid contact with eyes.
If contact occurs, flush thoroughly with water.

Directions

- Clean the skin thoroughly before applying this product.
- Shake to activate. Cover the entire affected area with a thin layer one to three times daily.
- Because excessive drying of the skin may occur, start with one application daily, then gradually increase to two or three times daily if needed or as directed by a doctor
- If bothersome dryness or peeling occurs, reduce application to once a day or every other day.

Other information

Avoid storing at extreme temperatures (below 40°F and above 100°F).

Inactive ingredients

Aqua (Water), Coco-Caprylate/Caprate, Glycerin, Propanediol, Cetyl Alcohol, Panthenol, Arachidyl Alcohol, C10-18 Triglycerides, Distarch Phosphate, Zinc PCA, Octadecenedioic Acid, Dimethicone, Benzyl Alcohol, Ammonium Acryloyldimethyltaurate/VP Copolymer, Potassium Cetyl Phosphate, Sodium Hydroxide, Behenyl Alcohol, Lactic Acid, Hydroxyacetophenone, Xanthan Gum, Arachidyl Glucoside, Sodium Lactate, Zinc Hydrolyzed Hyaluronate, Ethylhexylglycerin, Polysilicone-11, Sodium Hyaluronate, Tocopherol, Polylysine, Helianthus Annuus (Sunflower) Seed Oil.

Questions or Comments?

Call toll free (833) 981-2335